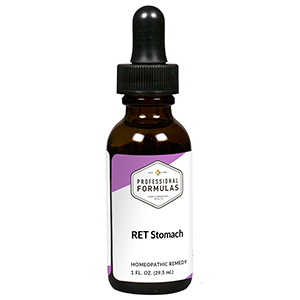 DRUG LABEL: RET Stomach
NDC: 63083-7001 | Form: LIQUID
Manufacturer: Professional Complementary Health Formulas
Category: homeopathic | Type: HUMAN OTC DRUG LABEL
Date: 20190815

ACTIVE INGREDIENTS: CICHORIUM INTYBUS FLOWER 3 [hp_X]/29.5 mL; MALUS SYLVESTRIS FLOWER 3 [hp_X]/29.5 mL; IMPATIENS GLANDULIFERA FLOWER 3 [hp_X]/29.5 mL; SALIX ALBA FLOWERING TOP 3 [hp_X]/29.5 mL; SILICON DIOXIDE 3 [hp_X]/29.5 mL; PULSATILLA MONTANA WHOLE 30 [hp_X]/29.5 mL; SULFUR 30 [hp_X]/29.5 mL
INACTIVE INGREDIENTS: ALCOHOL; WATER

RET1

ACTIVE INGREDIENTS

Chicory flower essence 3X
Crabapple flower essence 3X
Impatiens flower essence 3X
Willow flower essence 3X
Silicea 3X, 6X, 30X
Pulsatilla 30X, 100X, 200X
Sulphur 30X, 100X, 200X

QUESTIONS

Professional Formulas

PO Box 2034 Lake Oswego, OR 97035

INDICATIONS

Temporarily relieves impatience, being easily irritated, having poor self-image or the feeling of not being clean, resentment, being overly possessive, being easily offended, or being demanding or manipulative.*

PURPOSE

*Claims based on traditional homeopathic practice, not accepted medical evidence. Not FDA evaluated.

WARNINGS

In case of overdose, get medical help or contact a poison control center right away.

Keep out of the reach of children.

PREGNANCY OR BREAST FEEDING

If pregnant or breastfeeding, ask a healthcare professional before use.

DIRECTIONS

Place drops under tongue 30 minutes before/after meals. Adults and children 12 years and over: Take 5 drops up to 4 times per day for up to one month. Consult a physician for use in children under 12 years of age.

OTHER INFORMATION

Tamper resistant. If seal is broken, do not use. After opening, close container tightly and store at room temperature away from heat.

INACTIVE INGREDIENTS

20% ethanol, purified water.

LABEL

Est 1985

Professional Formulas

Complementary Health

RET Stomach

Homeopathic Remedy

1 FL. OZ. (29.5 mL)